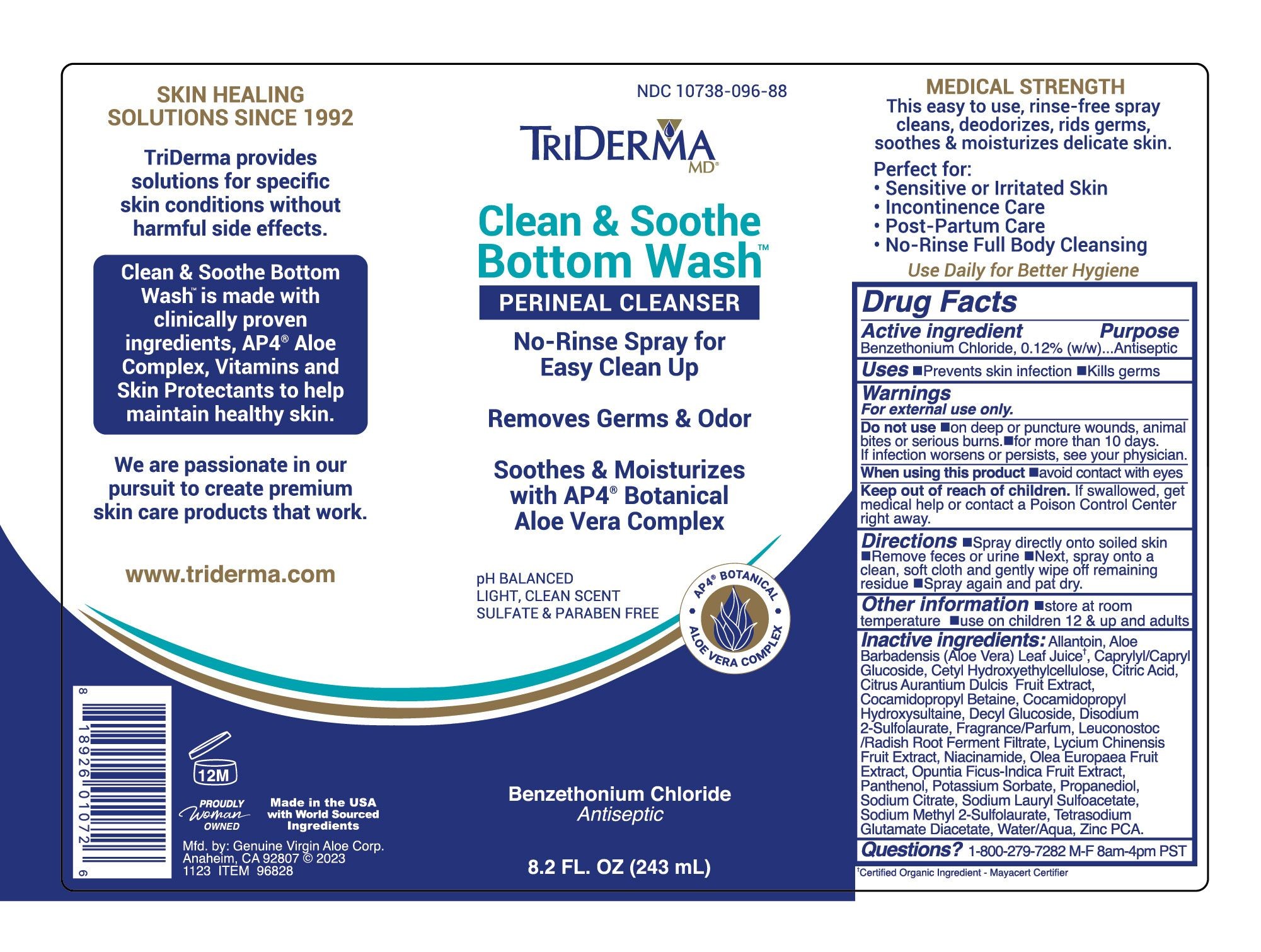 DRUG LABEL: TriDerma Clean Soothe Bottom Wash
NDC: 10738-096 | Form: LIQUID
Manufacturer: Genuine Virgin Aloe Corporation
Category: otc | Type: HUMAN OTC DRUG LABEL
Date: 20260129

ACTIVE INGREDIENTS: BENZETHONIUM CHLORIDE 0.0012 g/1 g
INACTIVE INGREDIENTS: ALOE VERA LEAF JUICE; ALLANTOIN

TriDerma Clean Soothe Bottom Wash

ACTIVE INGREDIENT

Benzethonium Chloride 0.12%

PURPOSE

Antiseptic

INDICATIONS AND USAGE

Prevents skin infection, removes germs

WARNINGS

for external use only

keep out of reach of children. if swallowed, get medical help or contact a poison control center right away.

DOSAGE AND ADMINISTRATION

Spray directly onto soiled skin. Remove feces or urine. Next, spray onto a clean, soft cloth and gently wipe off remaining residue. Spray again and pat dry.

STORAGE AND HANDLING

store at room temperature. use on children 12 & up and adults

INACTIVE INGREDIENT

Allantoin, Aloe Barbadensis (Aloe Vera) Leaf Juice†, Caprylyl/Capryl Glucoside, Cetyl Hydroxyethylcellulose, Citric Acid, Citrus Aurantium Dulcis Fruit Extract, Cocamidopropyl Betaine, Cocamidopropyl Hydroxysultaine, Decyl Glucoside, Disodium 2-Sulfolaurate, Fragrance/Parfum, Leuconostoc /Radish Root Ferment Filtrate, Lycium Chinensis Fruit Extract, Niacinamide, Olea Europaea Fruit Extract, Opuntia Ficus-Indica Fruit Extract, Panthenol, Potassium Sorbate, Propanediol, Sodium Citrate, Sodium Lauryl Sulfoacetate, Sodium Methyl 2-Sulfolaurate, Tetrasodium Glutamate Diacetate, Water/Aqua, Zinc PCA.

† Certified Organic Ingredient - Mayacert Certifier

KEEP OUT OF REACH OF CHILDREN

If swallowed get medical help or contact a Poison Control Center right away.